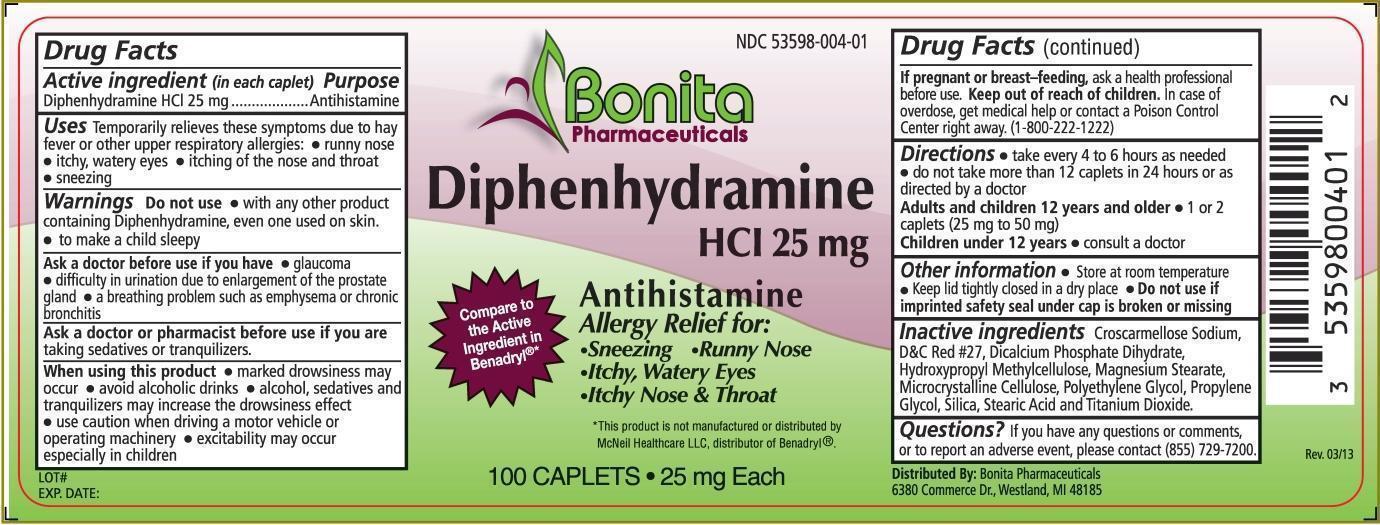 DRUG LABEL: Diphenhydramine Hydrochloride
NDC: 53598-004 | Form: TABLET, COATED
Manufacturer: Bonita Pharmaceuticals LLC
Category: otc | Type: HUMAN OTC DRUG LABEL
Date: 20130517

ACTIVE INGREDIENTS: Diphenhydramine Hydrochloride 25 mg/1 1
INACTIVE INGREDIENTS: CROSCARMELLOSE SODIUM; D&C RED NO. 27; DIBASIC CALCIUM PHOSPHATE DIHYDRATE; HYPROMELLOSES; MAGNESIUM STEARATE; CELLULOSE, MICROCRYSTALLINE; POLYETHYLENE GLYCOLS; PROPYLENE GLYCOL; SILICON DIOXIDE; STEARIC ACID; TITANIUM DIOXIDE

Diphenhydramine HCL 25mg Caplets

Active ingredient (in each Caplet)

Diphenhydramine HCl 25 mg

Purposes

Antihistamine

Uses

Temporarily relieves these symptoms due to hay fever or other upper respiratory allergies:

- runny nose
- itchy, watery eyes
- itching of the nose and throat
- sneezing

Warnings

Do not use

- with any other product containing diphenhydramine, even one used on skin.
- to make a child sleepy.

Ask a doctor before use if you have

- glaucoma
- difficulty in urinating due to an enlargement of the prostate gland
- a breathing problem such as emphysema or chronic bronchitis

Ask a doctor or pharmacist before use if you are

taking sedatives or tranquilizers.

When using this product

- marked drowsiness may occur
- avoid alcoholic drinks
- alcohol, sedatives, and tranquilizers may increase drowsiness effect
- use caution when driving a motor vehicle or operating machinery
- excitability may occur, especially in children

If pregnant or breast-feeding,

ask a health professional before use.

Keep out of reach of children.

In case of overdose,

get medical help or contact a Poison Control Center right away. (1-800-222-1222)

Directions

- take every 4 to 6 hours as needed
- do not take more than 6 times in 24 hours or as directed by a doctor

Adults and children 12 years and older

- 1 or 2 caplets (25mg to 50mg)

Children under 12 years

- ask a doctor

Other Information

- Store at room temperature
- keep lid tightly closed in dry place
- Do not use if imprinted safety seal under cap is broken or missing

Inactive Ingredients

Croscarmellose Sodium, D&C Red #27, Dicalcium Phosphate Dihydrate, Hydroxypropyle MethylCellulose, Magnesium Stearate, Microcrystalline Cellulose, Polyethylene Glycol, Propylene Glycol, Silica, Stearic Acid and Titanium Dioxide.

Questions?

If you have any questions or comments, or to report an adverse event, please contact (855) 729-7200.